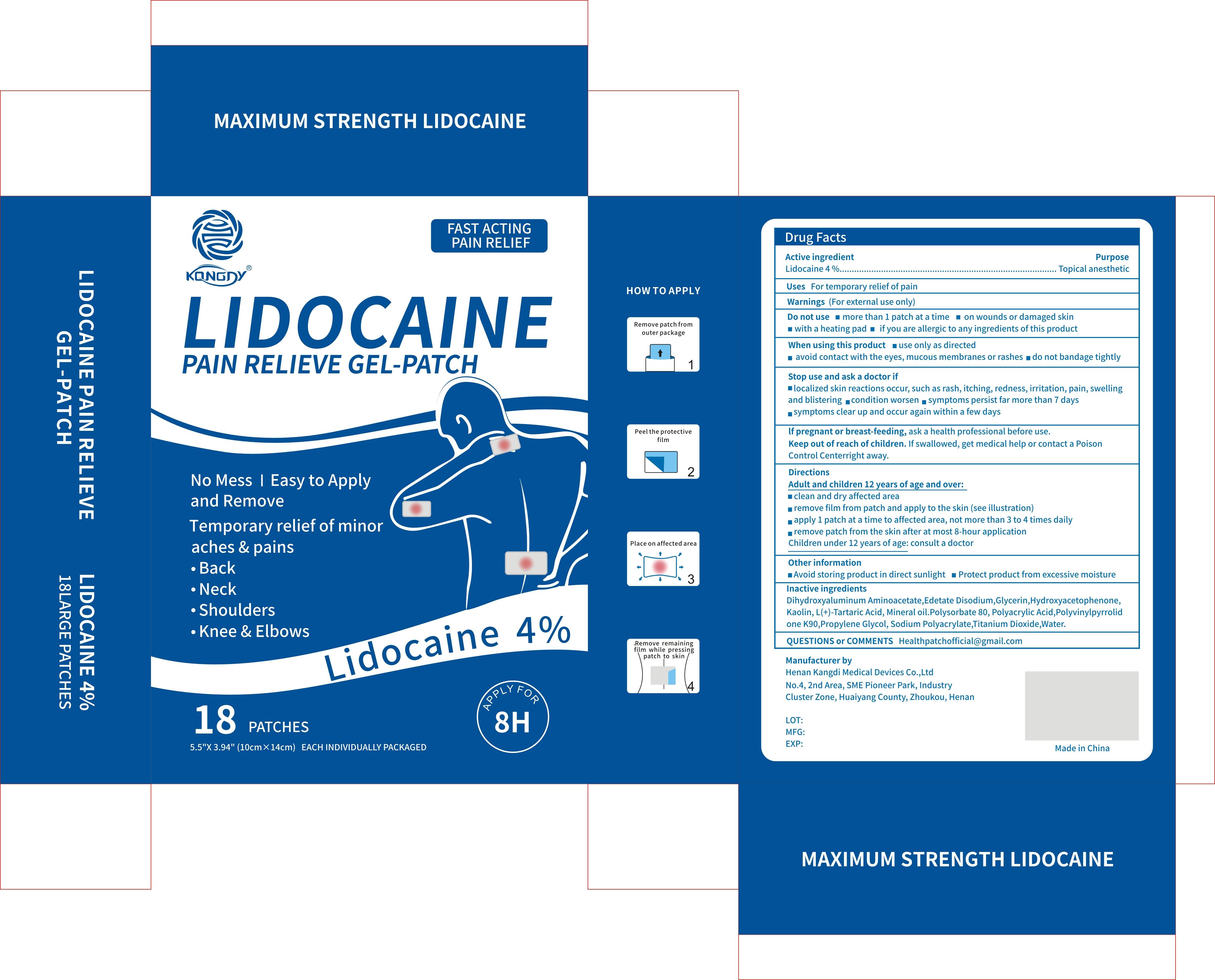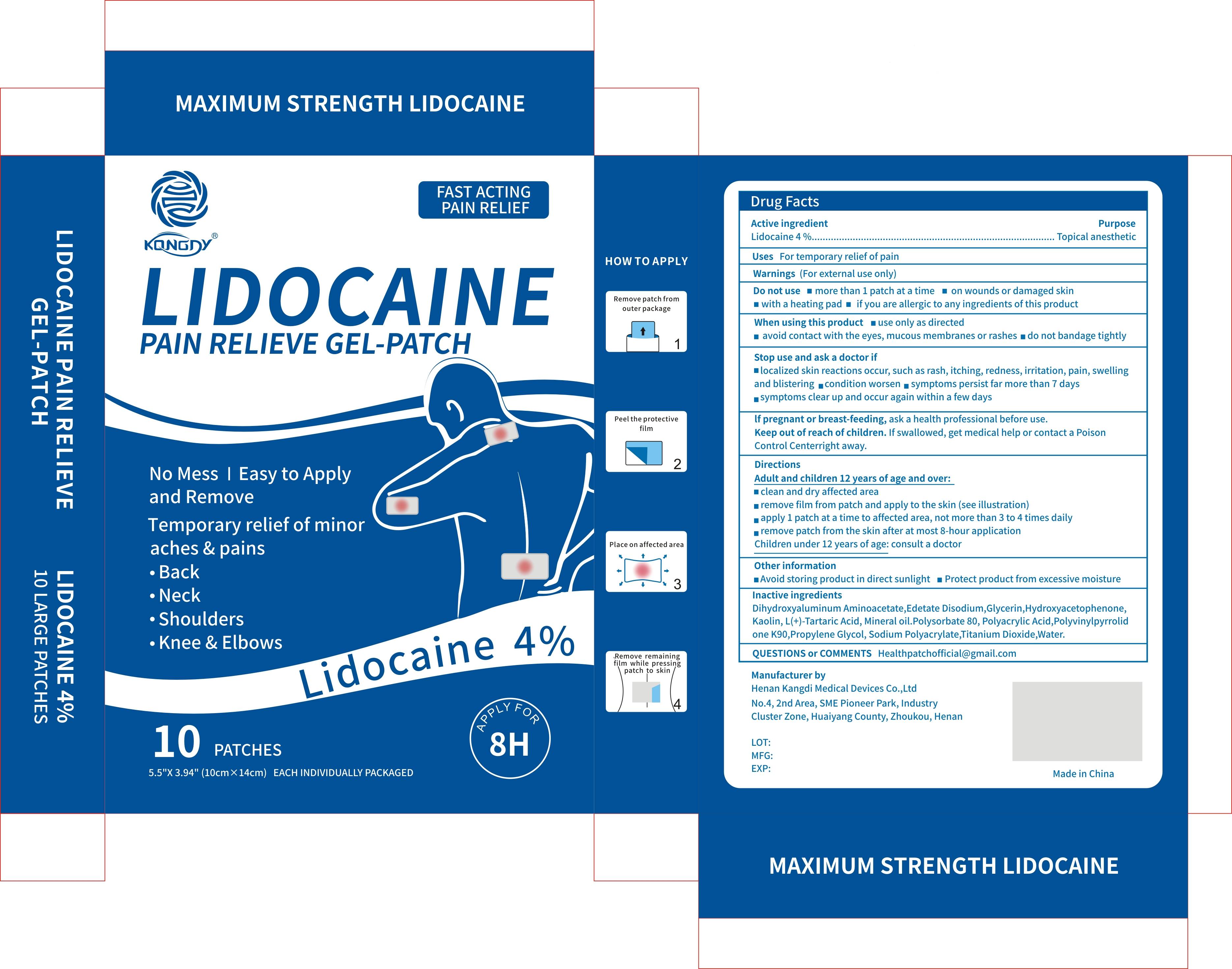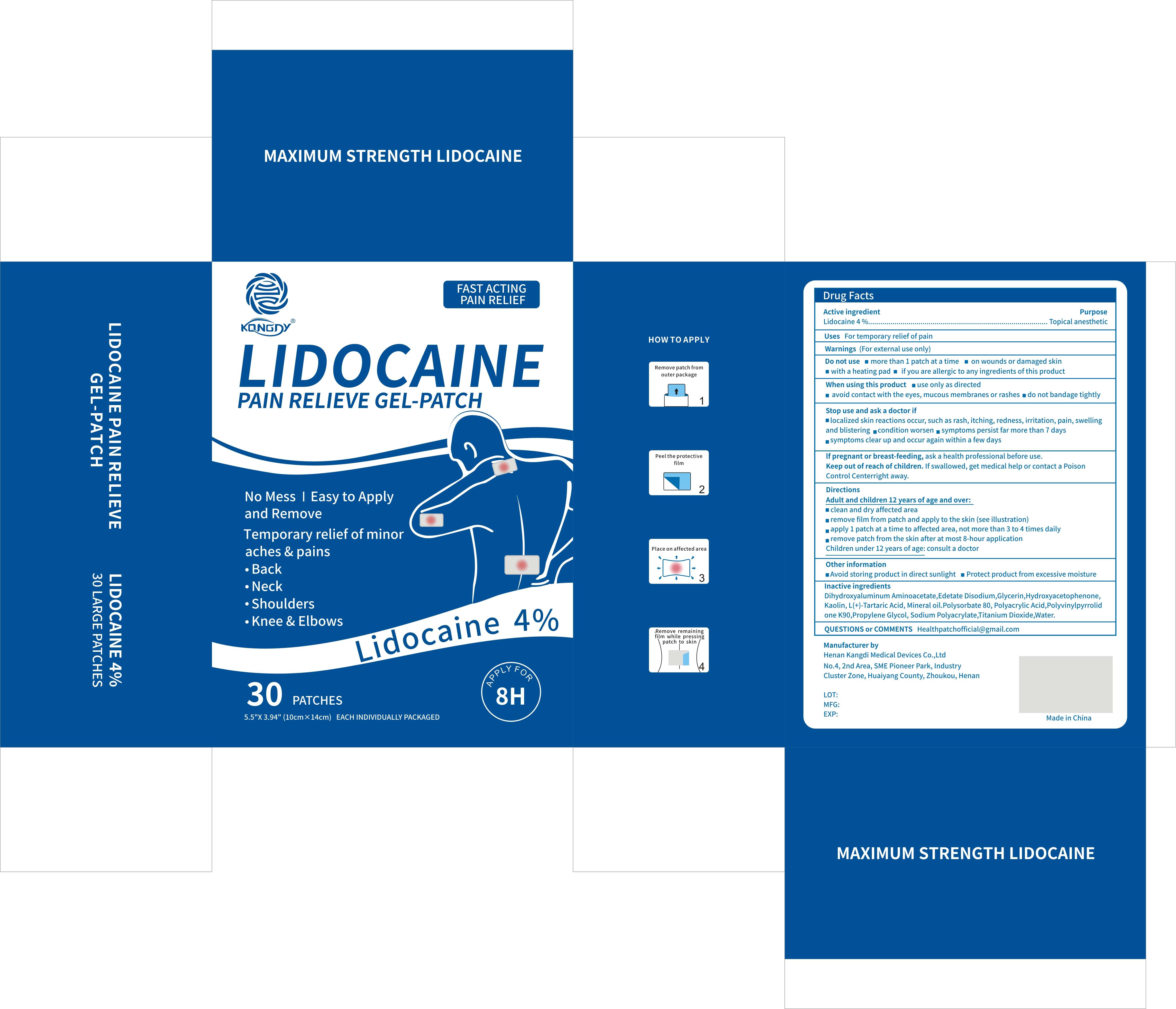 DRUG LABEL: Lidocaine Pain Relieve Gel-Patch
NDC: 69561-005 | Form: PATCH
Manufacturer: Henan Kangdi Medical Devices Co., Ltd
Category: otc | Type: HUMAN OTC DRUG LABEL
Date: 20260207

ACTIVE INGREDIENTS: LIDOCAINE 4 g/100 g
INACTIVE INGREDIENTS: SODIUM POLYACRYLATE (2500000 MW); POLYACRYLIC ACID (250000 MW); GLYCERIN; TARTARIC ACID; POVIDONE K90; WATER; KAOLIN; EDETATE DISODIUM; PROPYLENE GLYCOL; MINERAL OIL; POLYSORBATE 80; TITANIUM DIOXIDE; DIHYDROXYALUMINUM AMINOACETATE; HYDROXYACETOPHENONE

69561-005-01

Active Ingredient

LIDOCAINE 4%

Purpose

Topical Analgesic

Use

For temporary relief of pain

Warnings

For external use only

Do not use

■ more than 1 patch at a time
■ on wounds or damaged skin

■ with a heating pad

■ if you are allergic to any ingredients of this product

When Using

■ use only as directed
■ avoid contact with the eyes, mucous membranes, or rashes
■ do not bandage tightly

Stop Use

■ localized skin reactions occur, such as rash, itching, redness, irritation, pain, swelling and blistering
■ condition worsen
■ symptoms persist far more than 7 days
■ symptoms clear up and occur again within a few days

Ask Doctor

lf pregnant or breast-feeding

Keep Out Of Reach Of Children

If swallowed, get medical help or contact a Poison Control Centerright away.

Directions

Adult and children 12 years of age and over:
■ clean and dry affected area
■ remove film from patch and apply to the skin (see illustration)
■ apply 1 patch at a time to affected area, not more than 3 to 4 times daily
■ remove patch from the skin after at most 8-hour application
■ Children under 12 years of age: consult a doctor

Other information

■ Avoid storing product in direct sunlight
■ Protect product from excessive moisture

Inactive ingredients

Dihydroxyaluminum Aminoacetate,Edetate Disodium,Glycerin,Hydroxyacetophenone, Kaolin, L(+)-Tartaric Acid, Mineral oil.Polysorbate 80, Polyacrylic Acid,Polyvinylpyrrolidone K90,Propylene Glycol, Sodium Polyacrylate,Titanium Dioxide,Water.

Questions

Healthpatchofficial@gmail.com